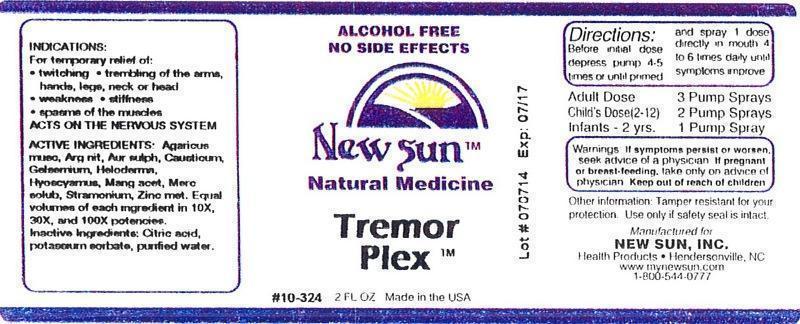 DRUG LABEL: Tremor Plex
NDC: 66579-0008 | Form: LIQUID
Manufacturer: New Sun Inc.
Category: homeopathic | Type: HUMAN OTC DRUG LABEL
Date: 20140821

ACTIVE INGREDIENTS: AMANITA MUSCARIA FRUITING BODY 10 [hp_X]/59 mL; SILVER NITRATE 10 [hp_X]/59 mL; GOLD MONOSULFIDE 10 [hp_X]/59 mL; CAUSTICUM 10 [hp_X]/59 mL; GELSEMIUM SEMPERVIRENS ROOT 10 [hp_X]/59 mL; HELODERMA HORRIDUM VENOM 10 [hp_X]/59 mL; HYOSCYAMUS NIGER 10 [hp_X]/59 mL; MANGANESE ACETATE TETRAHYDRATE 10 [hp_X]/59 mL; MERCURIUS SOLUBILIS 10 [hp_X]/59 mL; DATURA STRAMONIUM 10 [hp_X]/59 mL; ZINC 10 [hp_X]/59 mL
INACTIVE INGREDIENTS: CITRIC ACID MONOHYDRATE; POTASSIUM SORBATE; WATER

Tremor Plex

DOSAGE AND ADMINISTRATION

Directions: Before intial dose depress pump 4-5 times or until primed and spray 1 dose directly in mouth 4 to 6 times daily until symptoms improve.

Adult Dose: 3 Pump Sprays

Child's Dose (2-12): 2 Pump Sprays

Infants - 2 yrs: 1 Pump Sprays

WARNINGS

Warnings: If symptoms persist or worsen, seek advice of physician. If pregnant or breast-feeding, take only on advice of physician.

Keep out of reach of children.

Other information: Tamper resistant for your protection. Use only if safety seal is intact.

PURPOSE

Indications: For temporary relief of: •twitching •trembling of the arms, hands, legs, neck or head •weakness •stiffness •spasms of the muscles

ACTS ON THE NERVOUS SYSTEM

ACTIVE INGREDIENT

Active Ingredients: Agaricus muscarius, Argentum nitricum, Aurum sulphuratum, Causticum, Gelsemium sempervirens, Heloderma, Hyoscyamus niger, Manganum aceticum, Mercurius solubilis, Stramonium, Zincum metallicum. Equal volumes of each ingredient in 10X, 30X, and 100X potencies.

Inactive Ingredient: Citric acid, potassium sorbate, purified water.

Indications: For temporary relief of:

- twitching
- trembling of the arms, hands, legs, neck or head
- weakness
- stiffness
- spasms of the muscles

ACTS ON THE NERVOUS SYSTEM.